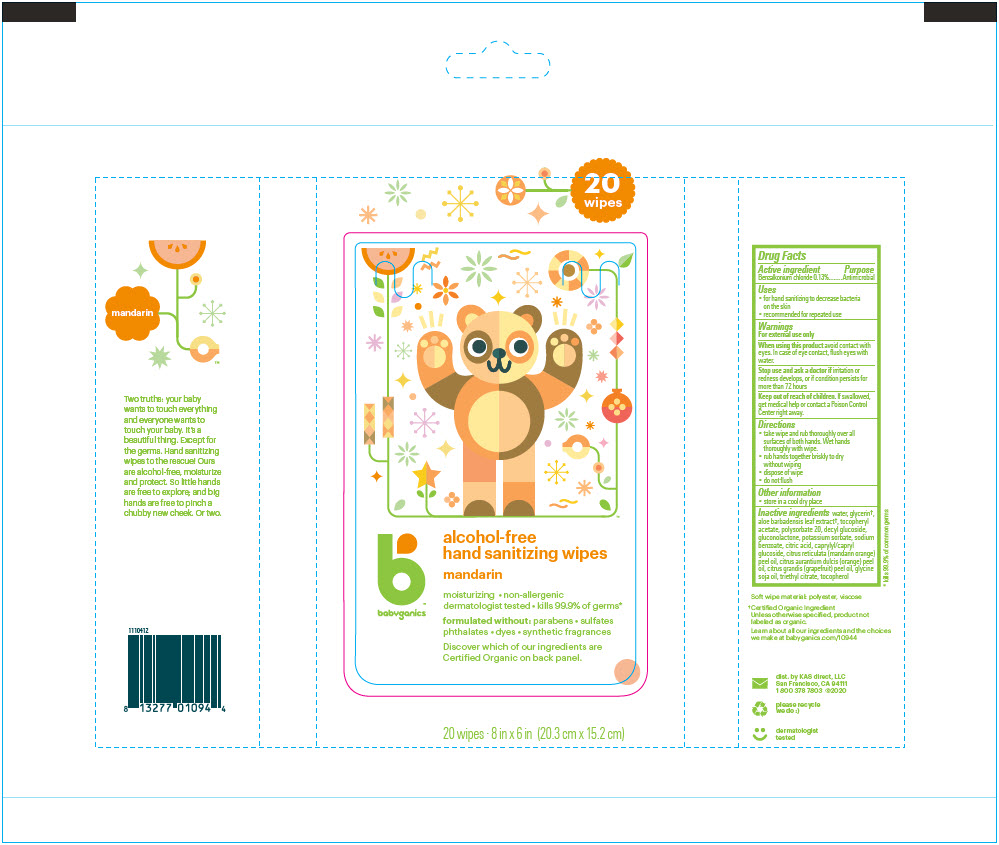 DRUG LABEL: BabyGanics Alcohol-Free Hand Sanitizer Wipes 
NDC: 59062-1094 | Form: CLOTH
Manufacturer: KAS Direct LLC dba BabyGanics
Category: otc | Type: HUMAN OTC DRUG LABEL
Date: 20200821

ACTIVE INGREDIENTS: BENZALKONIUM CHLORIDE 0.1 mg/1 mL
INACTIVE INGREDIENTS: WATER; GLUCONOLACTONE; DECYL GLUCOSIDE; GLYCERIN; POLYSORBATE 20; POTASSIUM SORBATE; SODIUM BENZOATE; CITRIC ACID MONOHYDRATE; ALOE VERA LEAF; .ALPHA.-TOCOPHEROL ACETATE

BabyGanics Alcohol-Free Hand Sanitizer Wipes
Mandarin

Drug Facts

Active ingredient

Benzalkonium chloride 0.13%

Purpose

Antimicrobial

Uses

- for hand sanitizing to decrease bacteria on the skin
- recommended for repeated use

Warnings

For external use only

When using this product avoid contact with eyes. In case of eye contact, flush eyes with water.

Stop use and ask a doctor if irritation or redness develops, or if condition persists for more than 72 hours

Keep out of reach of children. If swallowed, get medical help or contact a Poison Control Center right away.

Directions

- take wipe and rub thoroughly over all surfaces of both hands. Wet hands thoroughly with wipe.
- rub hands together briskly to dry without wiping
- dispose of wipe
- do not flush

Other information

- store in a cool dry place

Inactive ingredients

water, glycerin [Certified Organic Ingredient Unless otherwise specified, product not labeled as organic.] , aloe barbadensis leaf extract, tocopheryl acetate, polysorbate 20, decyl glucoside, gluconolactone, potassium sorbate, sodium benzoate, citric acid, caprylyl/capryl glucoside, citrus reticulata (mandarin orange) peel oil, citrus aurantium dulcis (orange) peel oil, citrus grandis (grapefruit) peel oil, glycine soja oil, triethyl citrate, tocopherol

dist. by KAS direct, LLC
San Francisco, CA 94111

PRINCIPAL DISPLAY PANEL - 20 Wipe Bag

20
wipes

babyganics

alcohol-free
hand sanitizing wipes

mandarin

moisturizing • non-allergenic
dermatologist tested • kills 99.9% of germs*

formulated without: parabens • sulfates
phthalates • dyes • synthetic fragrances

Discover which of our ingredients are
Certified Organic on back panel.

20 wipes ∙ 8 in x 6 in (20.3 cm x 15.2 cm)